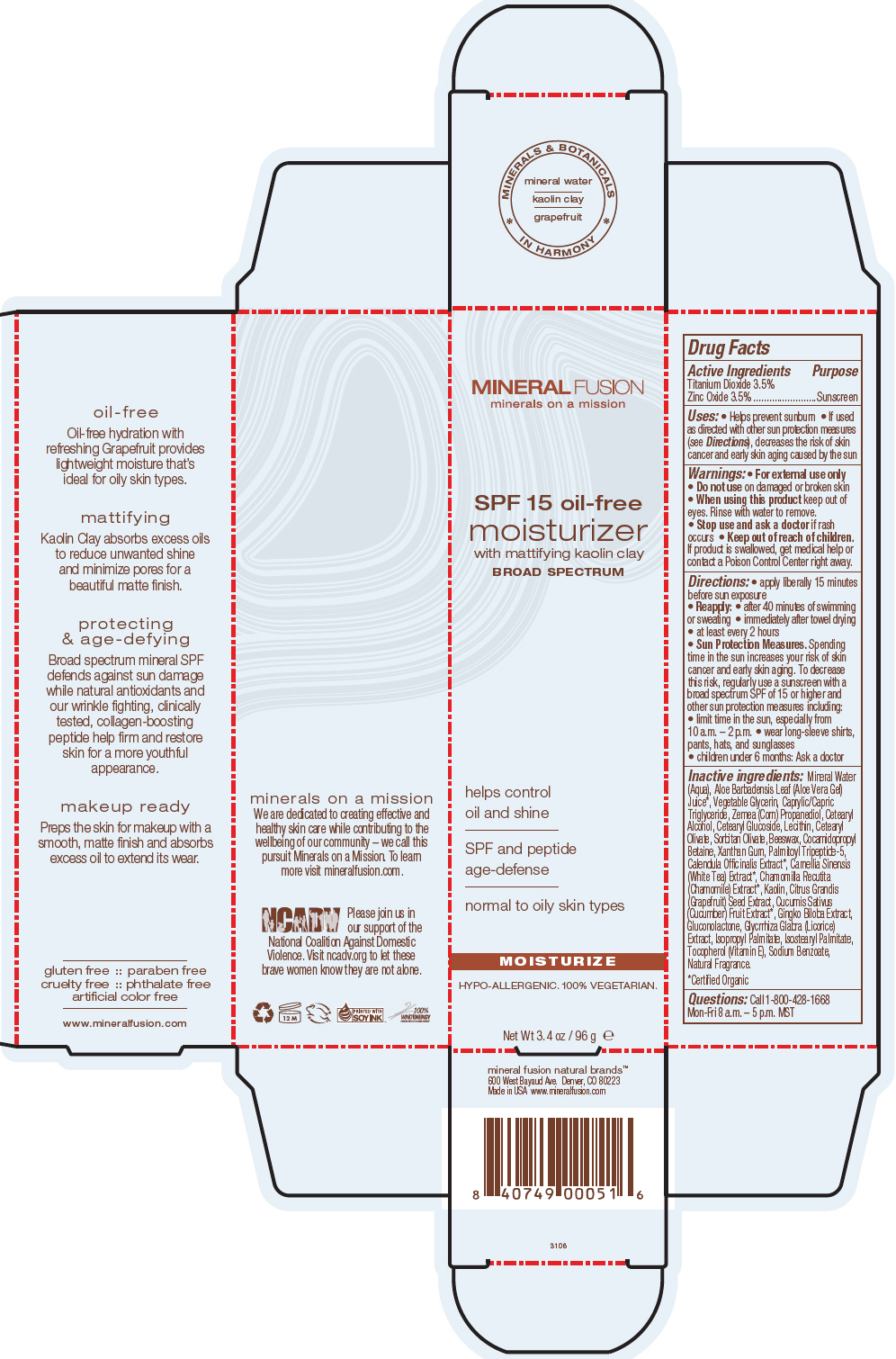 DRUG LABEL: MOISTURIZER SPF 15
NDC: 55789-3106 | Form: CREAM
Manufacturer: Mineral Fusion Natural Brands
Category: otc | Type: HUMAN OTC DRUG LABEL
Date: 20150821

ACTIVE INGREDIENTS: TITANIUM DIOXIDE 3.36 g/96 g; ZINC OXIDE 3.36 g/96 g
INACTIVE INGREDIENTS: WATER 67.2 g/96 g; ALOE VERA LEAF; GLYCERIN; MEDIUM-CHAIN TRIGLYCERIDES; PROPANEDIOL; CETEARYL OLIVATE; SORBITAN OLIVATE; YELLOW WAX; COCAMIDOPROPYL BETAINE; XANTHAN GUM; PALMITOYL TRIPEPTIDE-5; CALENDULA OFFICINALIS FLOWER; WHITE TEA; CHAMOMILE; KAOLIN; CITRUS PARADISI SEED; CUCUMBER; GINKGO; GLUCONOLACTONE; LICORICE; ISOPROPYL PALMITATE; ISOSTEARYL PALMITATE; TOCOPHEROL; SODIUM BENZOATE

OIL FREE MOISTURIZER SPF 15

Drug Facts

Active Ingredients

Titanium Dioxide 3.5%
Zinc Oxide 3.5%

Purpose

Sunscreen

Uses

- Helps prevent sunburn
- If used as directed with other sun protection measures (see Directions), decreases the risk of skin cancer and early skin aging caused by the sun

Warnings

- For external use only

- Do not use on damaged or broken skin

- When using this product keep out of eyes. Rinse with water to remove.

- Stop use and ask a doctor if rash occurs

- Keep out of reach of children. If product is swallowed, get medical help or contact a Poison Control Center right away.

Directions

- apply liberally 15 minutes before sun exposure
- Reapply:
  - after 40 minutes of swimming or sweating
  - immediately after towel drying
  - at least every 2 hours
- Sun Protection Measures. Spending time in the sun increases your risk of skin cancer and early skin aging. To decrease this risk, regularly use a sunscreen with a broad spectrum SPF of 15 or higher and other sun protection measures including:
  - limit time in the sun, especially from 10 a.m. – 2 p.m.
  - wear long-sleeve shirts, pants, hats, and sunglasses
- children under 6 months: Ask a doctor

Inactive ingredients

Mineral Water (Aqua), Aloe Barbadensis Leaf (Aloe Vera Gel) Juice [Certified Organic] , Vegetable Glycerin, Caprylic/Capric Triglyceride, Zemea (Corn) Propanediol, Cetearyl Alcohol, Cetearyl Glucoside, Lecithin, Cetearyl Olivate, Sorbitan Olivate, Beeswax, Cocamidopropyl Betaine, Xanthan Gum, Palmitoyl Tripeptide-5, Calendula Officinalis Extract, Camellia Sinensis (White Tea) Extract, Chamomilla Recutita (Chamomile) Extract, Kaolin, Citrus Grandis (Grapefruit) Seed Extract, Cucumis Sativus (Cucumber) Fruit Extract, Gingko Biloba Extract, Gluconolactone, Glycrrhiza Glabra (Licorice) Extract, Isopropyl Palmitate, Isostearyl Palmitate, Tocopherol (Vitamin E), Sodium Benzoate, Natural Fragrance.

Questions

Call 1-800-428-1668
Mon-Fri 8 a.m. – 5 p.m. MST

PRINCIPAL DISPLAY PANEL - 96 g Tube Carton

MINERAL FUSION
minerals on a mission

SPF 15 oil-free
moisturizer
with mattifying kaolin clay
BROAD SPECTRUM

helps control
oil and shine

SPF and peptide
age-defense

normal to oily skin types

MOISTURIZE

HYPO-ALLERGENIC. 100% VEGETARIAN.

Net Wt 3.4 oz / 96 g e